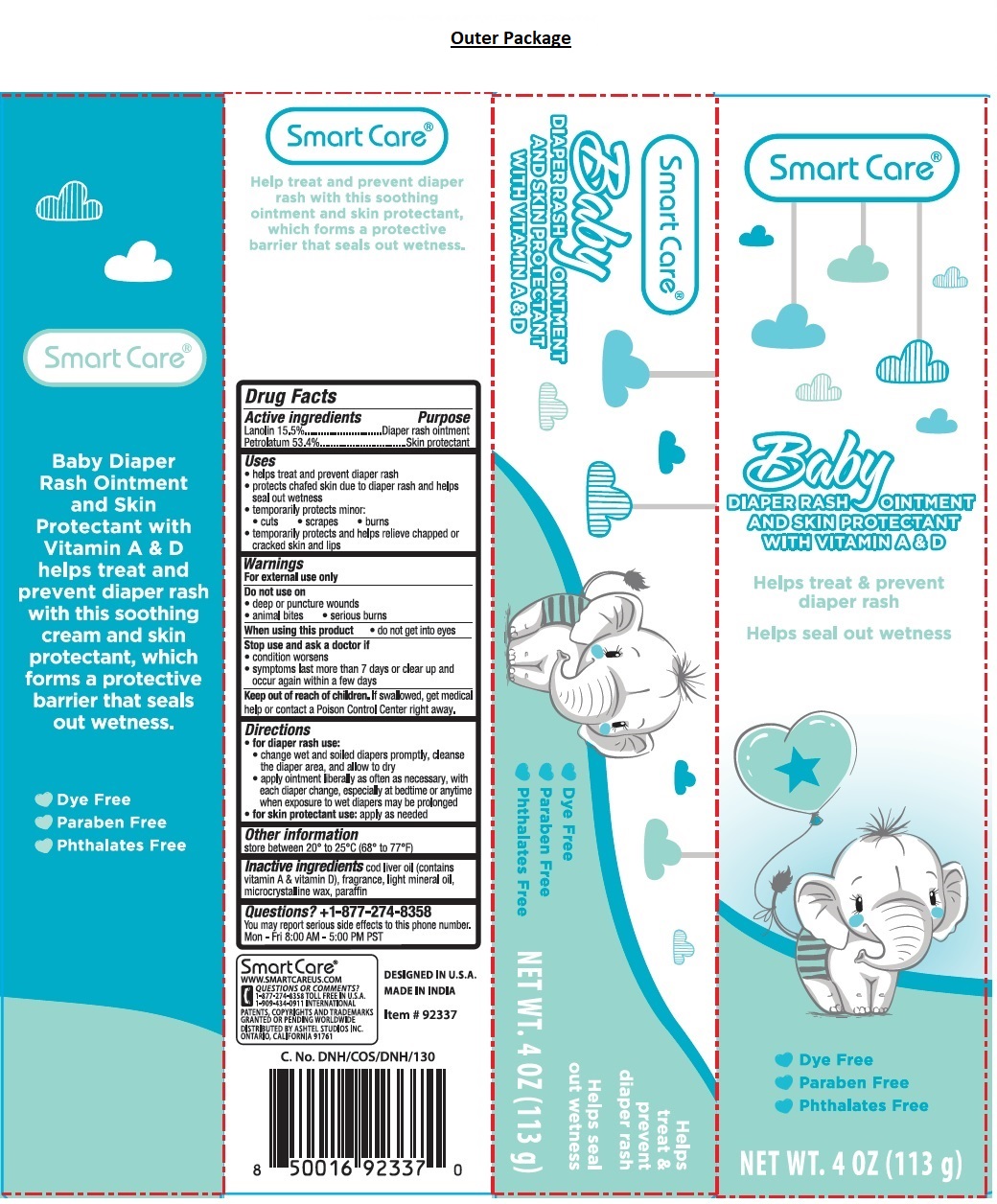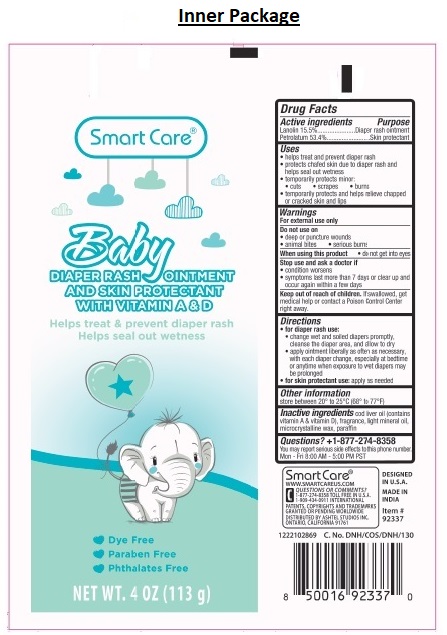 DRUG LABEL: Smart Care Baby Diaper Rash and Skin Protectant
NDC: 70108-073 | Form: OINTMENT
Manufacturer: Ashtel Studios, Inc
Category: otc | Type: HUMAN OTC DRUG LABEL
Date: 20210831

ACTIVE INGREDIENTS: LANOLIN 15.5 g/100 g; PETROLATUM 53.4 g/100 g
INACTIVE INGREDIENTS: COD LIVER OIL; LIGHT MINERAL OIL; MICROCRYSTALLINE WAX; PARAFFIN

Smart Care® Baby DIAPER RASH OINTMENT AND SKIN PROTECTANT

Active ingredients

Lanolin 15.5%

Petrolatum 53.4%

Purpose

Diaper rash ointment

Skin protectant

Uses

• helps treat and prevent diaper rash
• protects chafed skin due to diaper rash and helps seal out wetness
• temporarily protects minor:
• cuts • scrapes • burns
• temporarily protects and helps relieve chapped or cracked skin and lips

Warnings

For external use only

Do not use on
• deep or puncture wounds
• animal bites • serious burns

When using this product • do not get into eyes

Stop use and ask a doctor if
• condition worsens
• symptoms last more than 7 days or clear up and occur again within a few days

Keep out of reach of children. If swallowed, get medical help or contact a Poison Control Center right away.

Directions

• for diaper rash use:
• change wet and soiled diapers promptly, cleanse the diaper area, and allow to dry
• apply ointment liberally as often as necessary, with each diaper change, especially at bedtime or anytime when exposure to wet diapers may be prolonged
• for skin protectant use: apply as needed

Other information

store between 20° to 25°C (68° to 77°F)

Inactive ingredients

cod liver oil (contains vitamin A & vitamin D), fragrance, light mineral oil, microcrystalline wax, paraffin

Questions? +1-877-274-8358

You may report serious side effects to this phone number. Mon - Fri 8:00 AM - 5:00 PM PST

WITH VITAMIN A & D

Helps treat & prevent diaper rash with this soothing ointment and skin protectant, which forms a protective barrier that seals out wetness.

• Dye Free

• Paraben Free

• Phthalates Free

Smart Care®

WWW.SMARTCAREUS.COM

QUESTIONS OR COMMENTS?
1-877-274-8358 TOLL FREE IN U.S.A
1-909-434-0911 INTERNATIONAL

PATENTS, COPYRIGHTS AND TRADEMARKS GRANTED OR PENDING WORLDWIDE

DISTRIBUTED BY ASHTEL STUDIOS INC.
ONTARIO, CALIFORNIA 91761

DESIGNED IN U.S.A

MADE IN INDIA